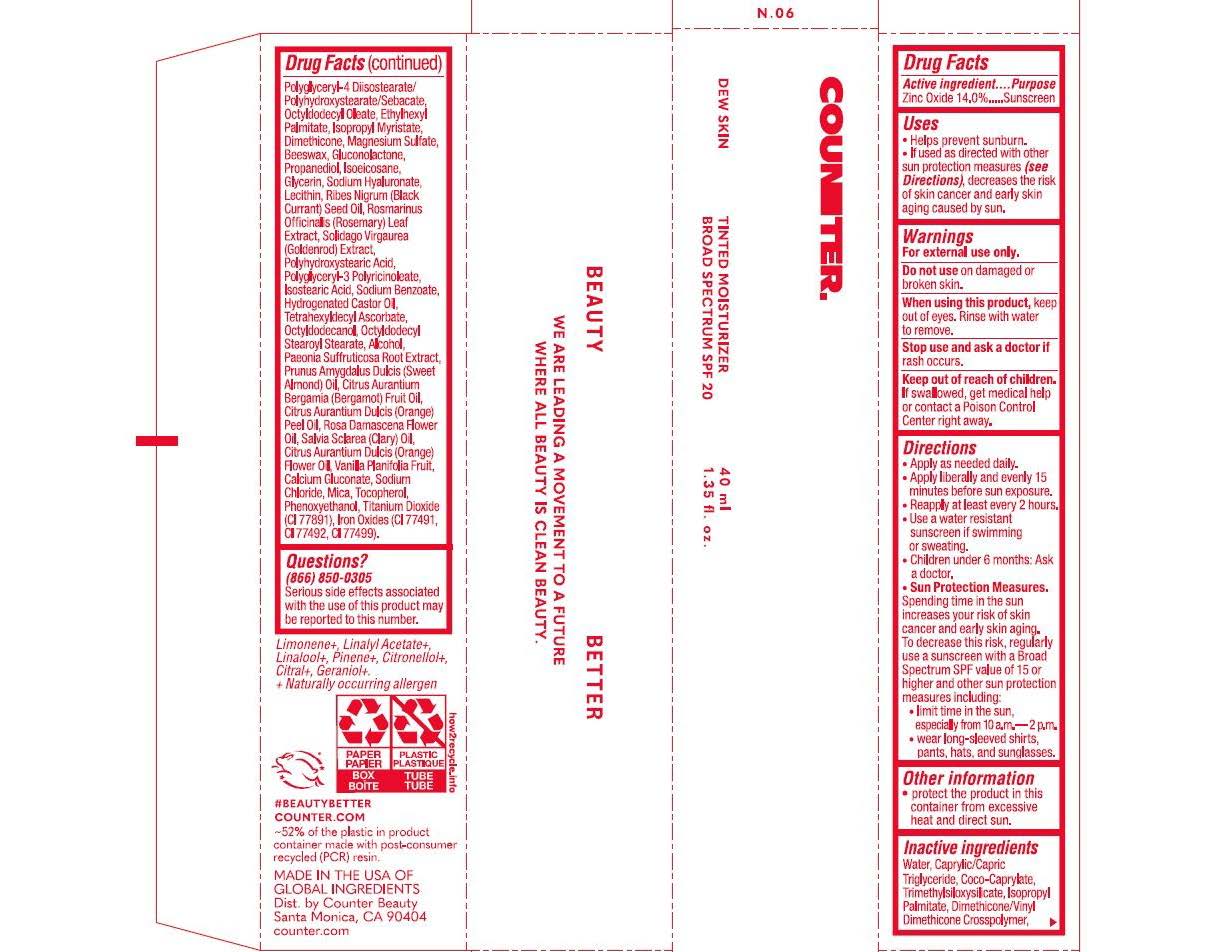 DRUG LABEL: Counter Beauty Dew Skin Tinted Moisturizer No. 6
NDC: 84435-106 | Form: LOTION
Manufacturer: G2G Ventures, PBC
Category: otc | Type: HUMAN OTC DRUG LABEL
Date: 20250718

ACTIVE INGREDIENTS: ZINC OXIDE 14 g/100 g
INACTIVE INGREDIENTS: PRUNUS AMYGDALUS DULCIS (SWEET ALMOND) OIL; SOLIDAGO VIRGAUREA WHOLE; ROSMARINUS OFFICINALIS (ROSEMARY) LEAF POWDER; DIMETHICONE 100; ISOPROPYL MYRISTATE; GLUCONOLACTONE; RIBES NIGRUM (BLACK CURRANT) SEED OIL; TRIMETHYLSILOXYSILICATE (M/Q 0.6-0.8); SODIUM CHLORIDE; HYDROGENATED CASTOR OIL; SODIUM BENZOATE; CALCIUM GLUCONATE; ISOSTEARIC ACID; OCTYLDODECYL STEAROYL STEARATE; CITRUS AURANTIUM DULCIS (ORANGE) FLOWER OIL; POLYHYDROXYSTEARIC ACID (2300 MW); TETRAHEXYLDECYL ASCORBATE; POLYGLYCERYL-3 RICINOLEATE; CI 77492; OCTYLDODECANOL; MAGNESIUM SULFATE; ISOEICOSANE; PROPANEDIOL; CI 77491; ETHYLHEXYL PALMITATE; COCO-CAPRYLATE; SODIUM HYALURONATE; BEESWAX; TITANIUM DIOXIDE; WATER; CITRUS AURANTIUM BERGAMIA (BERGAMOT) FRUIT OIL; MICA; LECITHIN, SOYBEAN; CITRUS AURANTIUM DULCIS (ORANGE) PEEL OIL; SALVIA SCLAREA (CLARY) OIL; ISOPROPYL PALMITATE; POLYGLYCERYL-4 DIISOSTEARATE/POLYHYDROXYSTEARATE/SEBACATE; OCTYLDODECYL OLEATE; ROSA DAMASCENA FLOWER OIL; TOCOPHEROL; CAPRYLIC/CAPRIC TRIGLYCERIDE; DIMETHICONE/VINYL DIMETHICONE CROSSPOLYMER (SOFT PARTICLE); GLYCERIN; ALCOHOL; PAEONIA SUFFRUTICOSA ROOT; VANILLA PLANIFOLIA FRUIT

Counter Beauty Dew Skin Tinted Moisturizer No. 6

ACTIVE INGREDIENT

Zinc Oxide 14.0%

PURPOSE

Sunscreen

INDICATIONS AND USAGE

- Helps prevent sunburn.
- If used as directed with other sun protection measures (see Directions), decreases the risk of skin cancer and early skin aging caused by the sun.

WARNINGS

For external use only.

DO NOT USE

On damaged or broken skin.

STOP USE

rash occurs.

WHEN USING

Keep out of eyes. Rinse with water to remove.

KEEP OUT OF REACH OF CHILDREN

If swallowed, get medical help or contaact a Poison Control Center right away.

DOSAGE AND ADMINISTRATION

- Apply as needed daily
- Apply liberally and evenly 15 minutes before sun exposure
- Reapply at least every 2 hours
- Use a water resistant sunscreen if swimming or sweating.
- Children under 6 months: Ask a doctor.
- Sun Protection Measures Spending time in the sun increases the risk of skin cancer and early skin aging. To decrease this risk, regularly use a sunscreen with a Broad Spectrum SPF value of 15 or higher and other sun protection measures including:
- limit time in the sun especially from 10 a.m. - 2 p.m.
- wear long- sleeved shirts, pants, hats, and sunglasses.

OTHER SAFETY INFORMATION

- Protect the product in this container from excessive heat or direct sun.

INACTIVE INGREDIENT

Water, Caprylic/Capric Triglyceride, Coco-Caprylate, Trimethylsiloxysilicate, Dimethicone/Vinyl Dimethicone Crosspolymer, Isopropyl Palmitate, Polyglyceryl-4 Diisostearate/Polyhydroxystearate/Sebacate, Octyldodecyl Oleate, Ethylhexyl Palmitate, Isopropyl Myristate, Dimethicone, Magnesium Sulfate, Beeswax, Gluconolactone, Glycerin, Isoeicosane, Propanediol, Hydrogenated Castor Oil, Sodium Chloride, Ribes Nigrum (Black Currant) Seed Oil, Octyldodecanol, Tetrahexyldecyl Ascorbate, Sodium Benzoate, Prunus Amygdalus Dulcis (Sweet Almond) Oil, Isostearic Acid, Lecithin, Polyglyceryl-3 Polyricinoleate, Polyhydroxystearic Acid, Octyldodecyl Stearoyl Stearate, Citrus Aurantium Bergamia (Bergamot) Fruit Oil, Alcohol, Citrus Aurantium Dulcis (Orange) Peel Oil, Paeonia Suffruticosa Root Extract, Calcium Gluconate, Rosa Damascena Flower Oil, Citrus Aurantium Dulcis (Orange) Oil, Salvia Sclarea (Clary) Oil, Vanilla Planifolia Fruit, Rosmarinus Officinalis (Rosemary) Leaf Extract, Solidago Virgaurea (Goldenrod) Extract ,Tocopherol ,Sodium Hyaluronate , May Contain (+/-): Titanium Dioxide (CI 77891) Yellow Iron Oxide (CI 77492) Iron Oxides (CI 77491) Iron Oxide (CI 77499), Mica (CI 77019)